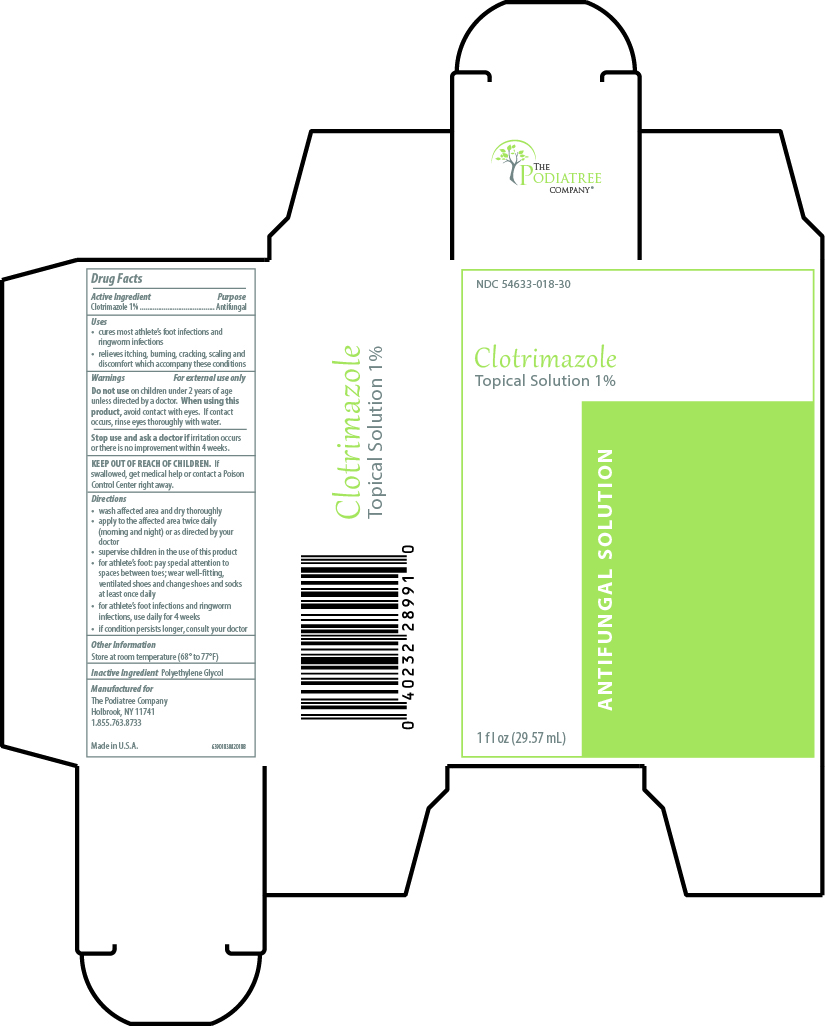 DRUG LABEL: Clotrimazole
NDC: 54633-018 | Form: SOLUTION
Manufacturer: The Podiatree Company
Category: otc | Type: HUMAN OTC DRUG LABEL
Date: 20260108

ACTIVE INGREDIENTS: CLOTRIMAZOLE 1 g/1 mL
INACTIVE INGREDIENTS: POLYETHYLENE GLYCOL 400

Clotrimazole Topical Solution USP,1%

Drug Facts

Active ingredient

Clotrimazole 1%

Purpose

Antifungal

Uses

- cures most athlete's foot infections and ringworm infections
- relieve itching,burning, cracking, scaling and discomfort which can accompany these conditions

Warnings

For external use only

Do not use on children under 2 years of age unless directed by a doctor.

When using this product avoid contact with eyes. If contact occurs, rinse eyes thoroughly with water.

Stop use and ask a doctor if irritation occurs or there is no improvement within 4 weeks.

KEEP OUT OF REACH OF CHILDREN. If swallowed, get medical help or contact a Poison Control Center right away.

Directions

• wash affected area and dry thoroughly

• apply to the affected area twice daily (morning and night) or as directed by your doctor

• supervise children in the use of this product

• for athlete’s foot: pay special attention to spaces between toes; wear well-fitting, ventilated shoes and change shoes and socks at least once daily

• for athlete’s foot and ringworm infections, use daily for 4 weeks

• if condition persists longer, consult your doctor

Inactive ingredient

polyethylene glycol

Other information

- Store at 20° to 25°C (68° to 77°F)

Questions?

1-855-763-8733

Manufactured for

The Podiatree Company, Holbrook, NY 11741

Made in U.S.A.